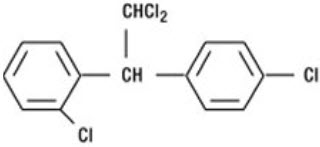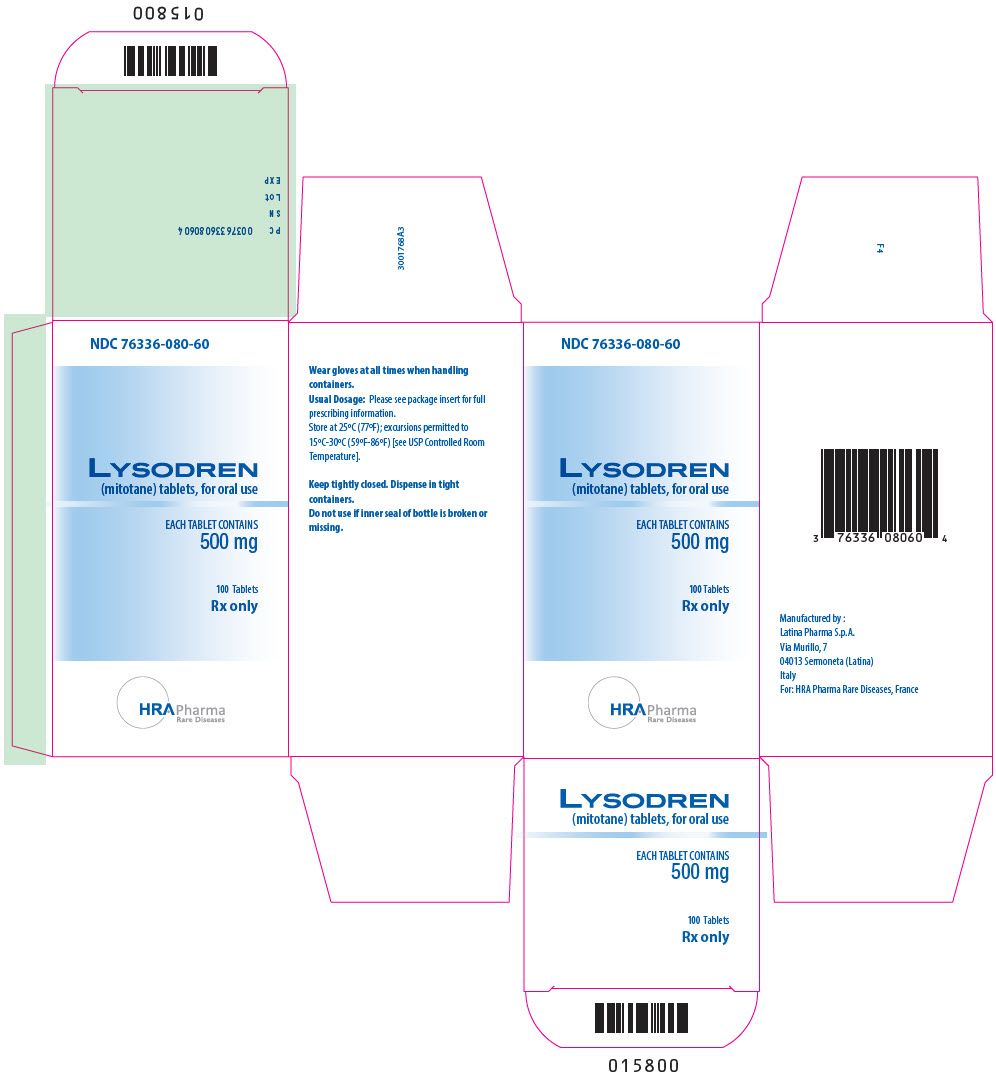 DRUG LABEL: Lysodren
NDC: 76336-080 | Form: TABLET
Manufacturer: HRA Pharma Rare Diseases
Category: prescription | Type: HUMAN PRESCRIPTION DRUG LABEL
Date: 20251008

ACTIVE INGREDIENTS: MITOTANE 500 mg/1 1
INACTIVE INGREDIENTS: MICROCRYSTALLINE CELLULOSE; POLYETHYLENE GLYCOL 3350; SILICON DIOXIDE; STARCH, CORN

HIGHLIGHTS OF PRESCRIBING INFORMATION

These highlights do not include all the information needed to use LYSODREN safely and effectively. See full prescribing information for LYSODREN.
LYSODREN®(mitotane) tablets, for oral use
Initial U.S. Approval: 1970

WARNING: ADRENAL CRISIS IN THE SETTING OF SHOCK, SEVERE TRAUMA OR INFECTION

See full prescribing information for complete boxed warning.

Patients treated with LYSODREN are at increased risk for developing adrenal crisis in the setting of shock, severe trauma or infection that may lead to death.

If shock, severe trauma or infection occurs or develops, temporarily discontinue LYSODREN and administer exogenous steroids. Monitor patients closely for infections and instruct patients to contact their physician immediately if injury, infection, or any other concomitant illness occurs (2.3, 5.1).

RECENT MAJOR CHANGES

BOXED WARNING | 01/2024
INDICATIONS AND USAGE (1) | 01/2024
DOSAGE AND ADMINISTRATION (2) | 01/2024
CONTRAINDICATIONS (4) | 01/2024
WARNINGS AND PRECAUTIONS (5) | 01/2024

1 INDICATIONS AND USAGE

LYSODREN is an adrenal cytotoxic agent indicated for the treatment of patients with inoperable, functional or nonfunctional, adrenocortical carcinoma (ACC). (1)

2 DOSAGE AND ADMINISTRATION

- The recommended initial dose of LYSODREN is 2000 mg to 6000 mg orally, in three or four divided doses per day with food. (2.3)
- Titrate LYSODREN dose to achieve a plasma level of 14 to 20 mg/L. (2.3)
- LYSODREN is lipophilic and accumulates in adipose tissue. (2.3)

3 DOSAGE FORMS AND STRENGTHS

Tablets: 500 mg, scored. (3)

4 CONTRAINDICATIONS

None. (4)

5 WARNINGS AND PRECAUTIONS

- Adrenal Insufficiency and Adrenal Crisis:Temporarily withhold LYSODREN during shock, trauma, infection or adrenal insufficiency. Steroid replacement may be necessary. (5.1)
- Central Nervous System (CNS) Toxicity: Monitor behavioral and neurologic assessments and mitotane plasma levels at regular intervals. Mitotane plasma levels exceeding 20 mg/L are associated with a greater incidence of toxicity. Advise patients not to drive or operate hazardous machinery if experiencing CNS adverse reactions. (5.2)
- Ovarian Macrocysts in Premenopausal Women: Monitor pelvic ultrasound at baseline and at regular intervals. Withhold, reduce the dose, or permanently discontinue LYSODREN based on severity. (5.3)
- Hepatotoxicity: Monitor liver functions tests prior to starting LYSODREN, during dose titration and as clinically indicated. Withhold, reduce the dose or permanently discontinue based on severity. (5.4)
- Hematologic Toxicity:Monitor complete blood counts prior to starting LYSODREN, during dose titration and as clinically indicated. Withhold, reduce the dose or permanently discontinue based on severity. (5.5)
- Prolonged Bleeding Time: Prolonged bleeding time has occurred in patients treated with mitotane and this should be taken into account when surgery is considered. (5.6)
- Embryo-Fetal Toxicity: Can cause fetal harm. Advise females of reproductive potential of the potential risk to a fetus and to use effective, nonhormonal contraception. (5.8)

6 ADVERSE REACTIONS

Most common adverse reactions include: anorexia, epigastric discomfort, nausea, vomiting, diarrhea, dizziness, vertigo, rash, hypercholesterolemia, hypertriglyceridemia, hypothyroidism, and decreased blood free testosterone in males. (6)

To report SUSPECTED ADVERSE REACTIONS, contact Direct Success Inc.at 1-844-597-6373 or FDA at 1-800-FDA-1088 or www.FDA.gov/medwatch.

7 DRUG INTERACTIONS

- Spironolactone:Avoid concomitant use with LYSODREN. (7.1)
- Certain CYP3A Substrates:Avoid concomitant use with LYSODREN. (7.2)
- Hormonal contraceptives:Avoid concomitant use with LYSODREN. (7.2)
- Warfarin:Avoid concomitant use with LYSODREN. (7.2)

8 USE IN SPECIFIC POPULATIONS

- Lactation:Advise not to breastfeed. (8.2)
- Hepatic Impairment:LYSODREN is not recommended for patients with severe hepatic impairment. In patients with mild to moderate hepatic impairment, monitor mitotane plasma levels frequently and modify the dosage as needed. (8.6)
- Renal Impairment: LYSODREN is not recommended for patients with severe renal impairment. In patients with mild or moderate renal impairment, monitor mitotane plasma levels frequently and modify the dosage as needed. (8.7)

FULL PRESCRIBING INFORMATION

WARNING: ADRENAL CRISIS IN THE SETTING OF SHOCK, SEVERE TRAUMA OR INFECTION

Patients treated with LYSODREN are at increased risk for developing adrenal crisis in the setting of shock, severe trauma or infection that may lead to death.

If shock, severe trauma or infection occurs or develops, temporarily discontinue LYSODREN and administer exogenous steroids. Monitor patients closely for infections and instruct patients to contact their physician immediately if injury, infection, or any other concomitant illness occurs [see Dosage and Administration (2.3) and Warnings and Precautions (5.1)].

1 INDICATIONS AND USAGE

LYSODREN is indicated for the treatment of patients with inoperable, functional or nonfunctional, adrenocortical carcinoma (ACC).

2 DOSAGE AND ADMINISTRATION

2.1 Recommended Evaluation and Testing Before Initiating LYSODREN

Before initiating LYSODREN, evaluate pelvic ultrasound in premenopausal women, liver functions tests and complete blood count [see Warnings and Precautions (5.3, 5.4, 5.5)].

2.2 General Precautions

LYSODREN is a hazardous drug. Advise caregivers to wear disposable gloves when handling LYSODREN tablets [see References (15)and Storage and Handling (16)].

2.3 Recommended Dosage and Administration

Recommended Dosage

- The recommended initial dose of LYSODREN is 2000 mg to 6000 mg orally, in three or four divided doses per day.
- Monitor mitotane plasma levels and increase the dose based on patient tolerance and clinical response incrementally to achieve a mitotane plasma level of 14 to 20 mg/L, or as tolerated. Consider monitoring mitotane plasma levels every 2 weeks after starting treatment and after each dose adjustment.
- The target plasma level is usually reached within a period of 3 to 5 months.
- Monitor mitotane plasma levels periodically (e.g., monthly). Severe neurotoxicity may occur with levels > 20 mg/L.

Dose Adjustments, Monitoring and Discontinuation

- In case of mitotane plasma levels above 20 mg/L without toxicities, consider reducing the dose by 50 to 75%.
- Monitor mitotane plasma levels regularly (e.g., every two months) after discontinuation of treatment. Due to the prolonged half-life, significant levels may persist for weeks after cessation of therapy.
- LYSODREN is lipophilic and accumulates in adipose tissue. Despite maintaining a constant dose, mitotane levels may suddenly increase. Monitor mitotane plasma levels even when LYSODREN has been withheld as adipose tissue may continue to release mitotane [see Clinical Pharmacology (12.3)] . Due to adipose tissue accumulation of mitotane, close monitoring of mitotane plasma levels is recommended in overweight patients and patients with recent weight loss.

Administration

- Swallow LYSODREN tablets whole; do not crush, chew or split.
- Take LYSODREN with food. Timing of the dose relative to meals must be consistent. Administration with high fat food enhances absorption [See Clinical Pharmacology Section (12.3)].
- Do not take tablets showing signs of deterioration.
- Caregivers should wear disposable gloves when handling the tablets. Avoid exposure to crushed and/or broken tablets. If contact with crushed/broken tablets occurs, wash the contaminated skin immediately and thoroughly.
- If a patient misses a dose, instruct the patient to take the next dose as scheduled.
- If a patient vomits after taking a dose, instruct the patient to take the next dose as scheduled.

2.4 Dosage Modifications for Adverse Reactions

The recommended dosage reduction for adverse reactions is to decrease the usual daily dose by 500 – 1000 mg.

Table 1 describes the dosage modifications for specific adverse reactions.

Table 1: Recommended Dosage Modifications for LYSODREN for Adverse Reactions
Adverse Reaction | Severity [Severity defined by National Cancer Institute Common Terminology Criteria for Adverse Events (NCI CTCAE) version 5.0.] | Dosage Modification
Adrenal Crisis and Adrenal Insufficiency [see Warnings and Precautions (5.1)] | All Grades | - Withhold LYSODREN during shock, trauma, infection or adrenal insufficiency until recovery to Grade ≤1 or baseline. - Resume LYSODREN at a reduced dose or permanently discontinue based on severity.
Central Nervous System (CNS) Toxicity [see Warnings and Precautions (5.2)] | Grade 2 | - Measure mitotane plasma level and modify the dosage according to the following recommendations: - Mitotane plasma level less than 14 mg/L: reduce the daily dose by 1000 mg. - Mitotane plasma level in the therapeutic window (14 to 20 mg/L): reduce the daily dose by 1500 mg. - Mitotane plasma level above 20 mg/L: withhold LYSODREN until recovery to grade ≤1 or baseline. Seven to ten (7-10) days after symptoms resolve, resume LYSODREN at reduced dose.
Central Nervous System (CNS) Toxicity [see Warnings and Precautions (5.2)] | Grade 3 or 4 | - Measure mitotane plasma level and modify the dosage according to the following recommendations: - Withhold LYSODREN until recovery to grade ≤ 1 or baseline. Seven to ten (7-10) days after symptoms resolve, resume LYSODREN at a reduced dose or permanently discontinue based on severity.
Gastrointestinal (GI) toxicity | Grade 3 or 4 | - Measure mitotane plasma level and modify the dosage according to the following recommendations: - Mitotane plasma level less than 14 mg/L: reduce the daily dose by 1000 mg. - Mitotane plasma level in the therapeutic window (14 to 20 mg/L): reduce the daily dose by 1500 mg. - Mitotane plasma level above 20 mg/L: withhold LYSODREN until recovery to grade ≤1 or baseline. - After symptoms resolve, resume LYSODREN at a reduced dose or permanently discontinue based on severity.
Hepatotoxicity [see Warnings and Precautions (5.4)] | Grade 3 or 4 | - Measure mitotane plasma level and modify the dosage according to the following recommendations: - Withhold LYSODREN until recovery to Grade ≤1 or baseline. - Resume at a reduced dose or permanently discontinue based on severity.
Hematologic Toxicity [see Warnings and Precautions (5.5)] | Grade 2 | - Measure mitotane plasma level and modify the dosage according to the following recommendations: - Withhold LYSODREN until recovery to Grade ≤1 or baseline. - Resume at the same dose.
Hematologic Toxicity [see Warnings and Precautions (5.5)] | Grade 3 or 4 | - Measure mitotane plasma level and modify the dosage according to the following recommendations: - Withhold LYSODREN until recovery to Grade ≤1 or baseline. - Resume at a reduced dose or permanently discontinue based on severity.
Other Adverse Reactions [see Adverse Reactions (6.1)] | Grade 2 | - Measure mitotane plasma level and modify the dosage according to the following recommendations: - Withhold LYSODREN until recovery to Grade ≤1 or baseline. - Resume at the same dose.
Other Adverse Reactions [see Adverse Reactions (6.1)] | Grade 3 or 4 | - Measure mitotane plasma level and modify the dosage according to the following recommendations: - Withhold LYSODREN until recovery to Grade ≤1 or baseline. - Resume at a reduced dose or permanently discontinue based on severity.

3 DOSAGE FORMS AND STRENGTHS

Tablets: 500 mg white, round, biconvex, scored tablets, bisected on one side and impressed with "BL" over "L1" on the other side.

4 CONTRAINDICATIONS

None.

5 WARNINGS AND PRECAUTIONS

5.1 Adrenal Insufficiency and Adrenal Crisis

Adrenal Insufficiency

LYSODREN can cause adrenal insufficiency or worsen existing adrenal insufficiency in patients with adrenocortical carcinoma.

Monitor for both glucocorticoid and mineralocorticoid insufficiency and replace systemic corticosteroids accordingly. Due to increased steroid clearance and increase of steroid-binding protein, high-dose replacement therapy may be required and free cortisol and corticotropin (ACTH) should be monitored to adapt the systemic corticosteroids.

Withhold, reduce the dose, or permanently discontinue LYSODREN based on severity [see Dosage and Administration (2.4)].

Adrenal Crisis in the Setting of Shock, Severe Trauma or Infection

LYSODREN can cause adrenal suppression and adrenal crisis in the setting of shock, severe trauma or infection.

Advise patients of the signs and symptoms of adrenal suppression and to contact their healthcare provider immediately if shock, trauma, infection, or adrenal suppression occurs. Withhold LYSODREN before planned surgeries.

Temporarily withhold LYSODREN during shock, trauma, infection or adrenal suppression [see Dosage and Administration (2.4)].

Provide supportive care and administer systemic corticosteroids until recovery.

5.2 Central Nervous System Toxicity

LYSODREN can cause central nervous system toxicity, including sedation, lethargy, and vertigo [see Adverse Reactions (6.1)].

Monitor behavioral and neurologic assessments and mitotane plasma levels at regular intervals. Mitotane plasma levels exceeding 20 mg/L are associated with a greater incidence of toxicity.

In cases of cognitive dysfunction, thyroid function should be evaluated as mitotane may induce hypothyroidism.

LYSODREN can impair the ability to drive and operate machinery. Advise patients not to drive or operate hazardous machinery if they are experiencing CNS adverse reactions. Withhold, reduce the dose, or permanently discontinue LYSODREN based on severity [see Dosage and Administration (2.4)].

5.3 Ovarian Macrocysts in Premenopausal Women

LYSODREN can cause non-malignant, multiple and bilateral ovarian macrocysts in premenopausal women.

Ovarian macrocysts can be symptomatic (e.g., pelvic pain or discomfort, or menstrual irregularities) or asymptomatic.

Complications from these cysts, including adnexal torsion and hemorrhagic cyst rupture, have occurred.

Advise female patients to contact their healthcare provider immediately for gynecological symptoms such as vaginal bleeding and/or pelvic pain [see Adverse Reactions (6.1)].

Monitor pelvic imaging in premenopausal females at baseline and in regular intervals during treatment with LYSODREN.

Withhold, reduce the dose, or permanently discontinue LYSODREN based on severity [see Dosage and Administration (2.4)].

5.4 Hepatotoxicity

LYSODREN can cause hepatoxicity, including liver injury or failure.

Monitor liver function tests prior to starting treatment with LYSODREN, during dose titration, and periodically during treatment as clinically indicated.

Isolated gamma-glutamyl transferase (GGT) elevation may occur.

Withhold, reduce the dose, or permanently discontinue LYSODREN based on severity of hepatoxicity [see Dosage and Administration (2.4)].

5.5 Hematologic toxicity

LYSODREN can cause leukopenia, anemia and thrombocytopenia [ see Adverse Reactions (6)] . Monitor complete blood counts including neutrophil count prior to starting treatment with LYSODREN, during dose titration, and periodically during treatment as clinically indicated. Withhold, reduce the dose, or permanently discontinue LYSODREN based on severity of cytopenia [see Dosage and Administration (2.4)] .

5.6 Prolonged Bleeding Time

LYSODREN can cause platelet function disorders due to abnormal adenosine diphosphate (ADP)-induced platelet aggregation. Some patients may have a prolonged bleeding time, while others may have a normal bleeding time.

Routine in vitro bleeding time is not suitable to detect this platelet defect and to assess bleeding risk.

Perform ADP-inducted platelet aggregometry testing prior to surgery or dental procedures to determine mitotane-induced bleeding risk. For patients with prolonged bleeding time, withhold or reduce the dose of LYSODREN as clinically indicated.

5.7 Hormone binding protein

Mitotane has been shown to increase plasma levels of hormone binding proteins (e.g., sex hormone-binding globulin (SHBG) and corticosteroid-binding globulin (CBG)). This should be taken into account when interpreting the results of hormonal assays and may result in gynecomastia.

5.8 Embryo-Fetal Toxicity

LYSODREN can cause fetal harm when administered to a pregnant woman. Abnormal pregnancy outcomes, such as preterm births and early pregnancy loss, can occur in patients exposed to mitotane during pregnancy. Advise pregnant women of the potential risk to a fetus. Advise females of reproductive potential to use effective nonhormonal contraception, during treatment with LYSODREN and after discontinuation of treatment for as long as mitotane plasma levels are detectable, since LYSODREN can render some hormonal contraceptives ineffective [see Drug Interactions (7.2), Use in Specific Populations (8.1, 8.3)].

6 ADVERSE REACTIONS

The following clinically significant adverse reactions are described elsewhere in the labeling:

• Adrenal Insufficiency and Adrenal Crisis [see Warnings and Precautions (5.1)]

• Central Nervous System Toxicity [see Warnings and Precautions (5.2)]

• Ovarian Macrocysts in Premenopausal Women [see Warnings and Precautions (5.3)]

• Hepatotoxicity [see Warnings and Precautions (5.4)]

• Hematologic Toxicity [see Warnings and Precautions (5.5)]

• Prolonged Bleeding Time [see Warnings and Precautions (5.6)]

• Hormone Binding Protein [see Warnings and Precautions (5.7)]

• Embryo-Fetal Toxicity [see Warnings and Precautions (5.8)]

6.1 Clinical Trials Experience

Because clinical trials are conducted under widely varying conditions, adverse reaction rates observed in the clinical trials of a drug cannot be directly compared to rates in the clinical trials of another drug and may not reflect the rates observed in practice.

Reported adverse reactions include:

- Metabolism and nutrition disorders: Anorexia
- Gastrointestinal disorders: Epigastric discomfort, nausea, vomiting, diarrhea, mucosal inflammation, dyspepsia
- Nervous system disorders: Dizziness, vertigo, confusion, headache, ataxia, mental impairment, weakness, dysarthria, paresthesia, polyneuropathy, movement disorder, balance disorder, dysgeusia
- Skin and subcutaneous tissue disorders: Rash, pruritus, hypersensitivity reactions
- Blood and lymphatic system disorders: Leukopenia, anemia, thrombocytopenia, prolonged bleeding time, hematuria, hemorrhagic cystitis
- Endocrine: Growth retardation, hypothyroidism
- Eye disorders: Maculopathy, visual blurring, diplopia, lens opacity, retinopathy
- Hepatobiliary disorders: Hepatitis, elevation of liver enzymes, liver injury (hepatocellular/cholestatic/mixed)
- Reproductive system and breast disorders: Gynecomastia, hypogonadism (in males)
- Investigations: Hypercholesterolemia, hypertriglyceridemia, decreased plasma androstenedione, decreased plasma testosterone in females, increased sex hormone binding globulin in females and males, decreased blood free testosterone in males, hypouricemia
- Musculoskeletal disorders: Muscular weakness, generalized aching
- General disorders: Fever
- Renal and urinary disorders: Albuminuria/proteinuria
- Vascular disorders: Hypertension, orthostatic hypotension, flushing
- Infections: Opportunistic infection
- Respiratory, thoracic and mediastinal disorders: Dyspnoea

7 DRUG INTERACTIONS

7.1 Effects of Other Drugs on LYSODREN

Spironolactone

Spironolactone may block the action of mitotane. Avoid concomitant use of mitotane with spironolactone [see Clinical Pharmacology (12.3)].

7.2 Effects of LYSODREN on Other Drugs

Certain CYP3A substrates

Mitotane is a strong CYP3A inducer. Concomitant use of LYSODREN may decrease the levels of CYP3A substrates, which may reduce the activity of these substrates [see Clinical Pharmacology (12.3)].

Avoid concomitant use of LYSODREN with other CYP3A substrates, where minimal level changes may lead to serious therapeutic failures. If concomitant use cannot be avoided, modify the dosage of the CYP3A substrate in accordance with the approved product labeling.

Hormonal Contraceptives

Avoid concomitant use of LYSODREN with hormonal contraceptives [see Warnings and Precautions (5.8), Use in Specific Populations (8.3)].

Warfarin

Mitotane may induce the metabolism of warfarin, which may reduce its level and its efficacy [see Clinical Pharmacology (12.3)] .

Avoid concomitant use of LYSODREN with warfarin. If concomitant use cannot be avoided, monitor INR more frequently and adjust warfarin dose as recommended in accordance with the recommendations in the warfarin Prescribing Information.

8 USE IN SPECIFIC POPULATIONS

8.1 Pregnancy

Risk Summary

LYSODREN can cause fetal harm. Limited postmarketing cases report preterm births and early pregnancy loss in women treated with LYSODREN during pregnancy. Animal reproduction studies have not been conducted with mitotane.

Advise pregnant women of the potential risk to a fetus.

In the U.S. general population, the estimated background risk of major birth defects and miscarriage in clinically recognized pregnancies is 2% to 4% and 15% to 20%, respectively.

8.2 Lactation

Risk Summary

Mitotane is excreted in human milk; however, the effect of LYSODREN on the breastfed child, or on milk production is unknown. Because of the potential for serious adverse reactions in a breastfed child, advise women not to breastfeed during treatment with LYSODREN and after discontinuation of treatment for as long as mitotane plasma levels are detectable.

8.3 Females and Males of Reproductive Potential

Pregnancy Testing

Verify the pregnancy status of females of reproductive potential prior to initiating LYSODREN [see Use in Specific Populations (8.1)] .

Contraception

LYSODREN can cause fetal harm when administered to a pregnant woman [see Use in Specific Populations (8.1)] .

Females

Advise females of reproductive potential to use effective nonhormonal contraception during treatment with LYSODREN and after discontinuation of therapy for as long as mitotane plasma levels are detectable [see Clinical Pharmacology (12.3)] . LYSODREN can render hormonal contraceptives ineffective [see Drug Interaction (7.2)] .

8.4 Pediatric Use

Effectiveness in pediatric patients has not been established.

Based on published case reports, mitotane may negatively impact neuro-psychological development (e.g., motor and speech delay, memory impairment) in children and adolescents. In cases of cognitive dysfunction, thyroid function should be evaluated as mitotane may induce hypothyroidism. Other effects of mitotane observed in pediatric patients that are cited in medical literature or in a pharmacovigilance database include growth delay and estrogenic-like effects such as uterine bleeding, breast development in females and gynecomastia in males.

8.5 Geriatric Use

Clinical studies of LYSODREN did not include sufficient numbers of patients aged 65 years and older to determine whether they respond differently than younger patients. Other reported clinical experience has not identified differences in responses between the older and younger patients. In general, dose selection for an older patient should be cautious, usually starting at the low end of the dosing range, reflecting the greater frequency of decreased hepatic, renal, or cardiac function, and of concomitant disease or other drug therapy.

8.6 Hepatic Impairment

Mitotane is metabolized through the liver and mitotane plasma levels may increase if liver function is impaired.

Because of the increased risk of adverse reactions in patients with mild or moderate hepatic impairment, monitor mitotane plasma levels more frequently and modify the dosage as needed [see Dosage and Administration (2.3)]. LYSODREN is not recommended for use in patients with severe hepatic impairment [see Warnings and Precautions (5.4)] .

8.7 Renal Impairment

Mitotane is eliminated through the kidney and mitotane plasma levels may increase if renal function is impaired.

Because of the increased risk of adverse reactions in patients with mild and moderate renal impairment, monitor mitotane plasma levels more frequently and modify the dosage as needed [see Dosage and Administration (2.4)]. LYSODREN is not recommended for use in patients with severe renal impairment.

10 OVERDOSAGE

LYSODREN overdosage (plasma levels are above 20 mg/L) can cause central nervous system toxicity, including sedation, lethargy, and vertigo, as well as muscular weakness and gait disturbance. Withhold LYSODREN as clinically indicated for signs or symptoms of toxicity.

LYSODREN is lipophilic and has a prolonged half-life; therefore, it may take weeks for plasma levels to decrease. LYSODREN is not likely to be dialyzable. Increase the frequency of mitotane plasma level monitoring, as clinically indicated.

11 DESCRIPTION

LYSODREN (mitotane) is an oral adrenal cytotoxic agent. The chemical name is (±)-1,1-dichloro-2-(o-chlorophenyl)-2-(p-chlorophenyl) ethane (also known as o,p'-DDD). The chemical structure is:

Mitotane is a white granular solid composed of clear colorless crystals. It is tasteless and has a slight pleasant aromatic odor. It is soluble in ethanol and has a molecular weight of 320.05.

Inactive ingredients in LYSODREN are: microcrystalline cellulose, polyethylene glycol 3350, silicon dioxide, and starch.

12 CLINICAL PHARMACOLOGY

12.1 Mechanism of Action

Mitotane is an adrenal cytotoxic agent with an unknown mechanism of action. Mitotane modifies the peripheral metabolism of steroids and directly suppresses the adrenal cortex. A reduction in 17-hydroxycorticosteroids in the absence of decreased corticosteroid levels and increased formation of 6-β-hydroxycortisol have been reported.

12.2 Pharmacodynamics

Mitotane exposure-response relationships and the time course of pharmacodynamic response have not been fully characterized.

12.3 Pharmacokinetics

Absorption

Following oral administration of LYSODREN, 40% of the dose is absorbed.

Effect of Food

The effect of food on the absorption of mitotane (LYSODREN) is not known.

High fat food: Data with various mitotane formulations suggest that administration with high fat food enhances absorption of mitotane.

Distribution

Mitotane is found in most tissues of the body; however, fat is the primary site of distribution.

Elimination

Following discontinuation of mitotane, the plasma terminal half-life ranges from 18 to 159 days (median 53 days).

Metabolism

Mitotane is converted to a water-soluble metabolite. Mitotane metabolism includes hepatic and extrahepatic metabolism. Mitotane is metabolized to 1,1-(o,p'-dichlorodiphenyl) acetic acid (o,p'-DDA), as the major circulating metabolite.

Excretion

No unchanged mitotane is found in urine or bile. Approximately 10% of the administered dose is recovered in the urine as a water-soluble metabolite. A variable amount of metabolite (1%-17%) is excreted in the bile.

Specific Populations

Patients with Hepatic or Renal Impairment

The pharmacokinetics of mitotane have not been studied in patients with hepatic impairment or patients with renal impairment.

Drug Interaction Studies

Effects of Mitotane on Other Drugs

Midazolam:Coadministration of a single dose of midazolam (CYP3A substrate) in patients who received LYSODREN resulted in decreased midazolam concentrations relative to patients who had not received LYSODREN.

Spironolactone: The effect of concomitant spironolactone on the pharmacokinetics of mitotane has not been studied; however, patients exhibited significantly lower mitotane levels compared to those who did not receive concomitant spironolactone despite receiving higher mitotane doses.

13 NONCLINICAL TOXICOLOGY

13.1 Carcinogenesis, Mutagenesis, Impairment of Fertility

The carcinogenicity and mutagenicity of mitotane are unknown. Fertility studies have not been conducted with mitotane.

15 REFERENCES

1. OSHA Hazardous Drugs .http://www.osha.gov/hazardous-drugs/

16 HOW SUPPLIED/STORAGE AND HANDLING

LYSODREN tablets are supplied as 500 mg white, round, biconvex, scored tablets, bisected on one side and impressed with "BL" over "L1" on the other side.

- 100 tablets per bottle: NDC 76336-080-60

STORAGE AND HANDLING

Store bottles at 25°C (77°F); excursions permitted between 15°C and 30°C (59°F-86°F).

Mitotane is a hazardous drug. Follow applicable special handling and disposal procedures [see References (15)] .

17 PATIENT COUNSELING INFORMATION

Advise the patient to read the FDA-approved patient labeling (Medication Guide).

Adrenal Insufficiency and Adrenal Crisis

• Advise patients of the risk of adrenal suppression that may require steroid treatment and interruption or discontinuation of LYSODREN [see Warnings and Precautions (5.1)].

• Advise patients to discontinue LYSODREN in the case of shock, severe trauma or infection and contact their healthcare provider immediately [see Warnings and Precautions (5.1)].

• Advise patients to inform their healthcare provider of any planned surgeries [see Warnings and Precautions (5.1)].

Central Nervous System Toxicity

• Advise patients to contact their healthcare provider if they experience new or worsening symptoms of central nervous system (CNS) toxicity including sedation, lethargy and vertigo [see Warnings and Precautions (5.2)].

• Instruct patients not to drive or operate hazardous machinery if they are experiencing CNS adverse reactions [see Warnings and Precautions (5.2)].

Ovarian Macrocysts in Premenopausal Women

• Advise premenopausal women that their healthcare provider will monitor them with routine imaging and to contact their healthcare provider if they experience gynecological symptoms such as vaginal bleeding and/or pelvic pain [see Warnings and Precautions (5.3)].

Hepatotoxicity

• Advise patients that their healthcare provider will monitor them with laboratory tests to monitor liver function and to immediately contact their healthcare provider to report signs and symptoms of hepatotoxicity [see Warnings and Precautions (5.4)].

Hematologic Toxicity

• Advise patients to immediately contact their healthcare provider for fever, other signs of infection, unusual bruising, bleeding, tiredness or pallor [see Warnings and Precautions (5.5)].

Prolonged Bleeding Time

• Advise patients of the possibility of prolonged bleeding time while taking LYSODREN and of the need to withhold LYSODREN if surgery or dental procedures are needed [see Warnings and Precautions (5.6)].

• Advise patients to inform their healthcare provider of any planned surgeries or dental procedures [see Warnings and Precautions (5.6)].

• Advise patients to contact their healthcare provider for bruising or bleeding [see Warnings and Precautions (5.6)].

Embryo-Fetal Toxicity

• Advise females of reproductive potential of the potential risk to a fetus and to inform their healthcare provider of a known or suspected pregnancy [see Warnings and Precautions (5.8) and Use in Specific Populations (8.1)].

Females of Reproductive Potential

• Advise females of reproductive potential to use effective nonhormonal contraception during treatment with LYSODREN and after discontinuation of treatment for as long as mitotane plasma levels are detectable, since LYSODREN can render some hormonal contraceptives ineffective [see Drug Interactions (7.2), Use in Specific Populations (8.3)].

Lactation

• Advise females not to breastfeed during treatment with LYSODREN [see Use in Specific Populations (8.2)].

Drug Interactions

• Advise patients and their caregivers to inform their healthcare providers of all concomitant medications, herbal and dietary supplements [see Drug Interactions (7.1, 7.2)].

Address medical inquiries to:

Direct Success Inc.

1710 Hwy 34

Farmingdale, NJ 07727

1-844-597-6373

Fax: 1-855-674-6767

Manufactured by:

Latina Pharma S.p.A.

Via Murillo, 7

04013 Sermoneta (Latina)

Italy

For: HRA Pharma Rare Diseases

Advise the patient to read the FDA-approved patient labeling (Medication Guide).

Adrenal Insufficiency and Adrenal Crisis

- Advise patients of the risk of adrenal suppression that may require steroid treatment and interruption or discontinuation of LYSODREN [see Warnings and Precautions (5.1)].
- Advise patients to discontinue LYSODREN in the case of shock, severe trauma or infection and contact their healthcare provider immediately [see Warnings and Precautions (5.1)].
- Advise patients to inform their healthcare provider of any planned surgeries [see Warnings and Precautions (5.1)].

Central Nervous System Toxicity

- Advise patients to contact their healthcare provider if they experience new or worsening symptoms of central nervous system (CNS) toxicity including sedation, lethargy and vertigo [see Warnings and Precautions (5.2)].
- Instruct patients not to drive or operate hazardous machinery if they are experiencing CNS adverse reactions [see Warnings and Precautions (5.2)].

Ovarian Macrocysts in Premenopausal Women

- Advise premenopausal women that their healthcare provider will monitor them with routine imaging and to contact their healthcare provider if they experience gynecological symptoms such as vaginal bleeding and/or pelvic pain [see Warnings and Precautions (5.3)] .

Hepatotoxicity

- Advise patients that their healthcare provider will monitor them with laboratory tests to monitor liver function and to immediately contact their healthcare provider to report signs and symptoms of hepatotoxicity [see Warnings and Precautions (5.4)].

Hematologic Toxicity

- Advise patients to immediately contact their healthcare provider for fever, other signs of infection, unusual bruising, bleeding, tiredness or pallor [ see Warnings and Precautions (5.5)].

Prolonged Bleeding Time

- Advise patients of the possibility of prolonged bleeding time while taking LYSODREN and of the need to withhold LYSODREN if surgery or dental procedures are needed [see Warnings and Precautions (5.6)].
- Advise patients to inform their healthcare provider of any planned surgeries or dental procedures [see Warnings and Precautions (5.6)].
- Advise patients to contact their healthcare provider for bruising or bleeding [see Warnings and Precautions (5.6)].

Embryo-Fetal Toxicity

- Advise females of reproductive potential of the potential risk to a fetus and to inform their healthcare provider of a known or suspected pregnancy [see Warnings and Precautions (5.8)and Use in Specific Populations (8.1)] .

Females of Reproductive Potential

- Advise females of reproductive potential to use effective nonhormonal contraception during treatment with LYSODREN and after discontinuation of treatment for as long as mitotane plasma levels are detectable, since LYSODREN can render some hormonal contraceptives ineffective [see Drug Interactions (7.2), Use in Specific Populations (8.3)].

Lactation

- Advise females not to breastfeed during treatment with LYSODREN [see Use in Specific Populations (8.2)] .

Drug Interactions

- Advise patients and their caregivers to inform their healthcare providers of all concomitant medications, herbal and dietary supplements [see Drug Interactions (7.1, 7.2)].

Address medical inquiries to:
Direct Success Inc.
1710 Hwy 34
Farmingdale, NJ 07727
1-844-597-6373
Fax: 1-855-674-6767

Manufactured by:
Latina Pharma S.p.A.
Via Murillo, 7
04013 Sermoneta (Latina)
Italy

For: HRA Pharma Rare Diseases

MEDICATION GUIDE

LYSODREN® (LY-SO-DREN)

(mitotane)

tablets, for oral use

What is the most important information I should know about LYSODREN?

LYSODREN can cause serious side effects including:

Adrenal Insufficiency and Adrenal Crisis.

Adrenal Insufficiency. LYSODREN can cause your adrenal glands to stop making enough corticosteroid hormones (adrenal insufficiency) or make this problem worse in people with cancer of the adrenal glands (adrenocortical carcinoma). Your healthcare provider may temporarily stop, reduce your dose, or permanently stop treatment with LYSODREN if you develop adrenal insufficiency during treatment.

Adrenal Crisis. LYSODREN can cause your adrenal glands to suddenly stop making enough corticosteroid hormones (adrenal crisis). You are at increased risk for developing adrenal crisis if you experience shock, severe injury, or infection during treatment with LYSODREN. Adrenal crisis may lead to death. Tell your healthcare provider right away if you get an injury, infection, or other illness during treatment with LYSODREN. Your healthcare provider will temporarily stop LYSODREN if shock, severe injury, or infections happen during treatment. Tell your healthcare provider if you have any planned surgery.

Your healthcare provider will check your levels of corticosteroid hormones during treatment and may give you corticosteroid medicine if you develop adrenal gland problems. Tell your healthcare provider right away if you develop any signs or symptoms of adrenal gland problems, including:

severe weakness
confusion
pain in the lower back and legs
stomach (abdominal) pain
nausea, vomiting, or diarrhea

feeling lightheaded or dizzy
passing out
feeling very tired
decreased appetite
weight loss

areas of darkened skin
craving salt
low blood sugar
feeling irritable or depressed
hair loss

See "What are the possible side effects of LYSODREN?" for more information about side effects.

What is LYSODREN?

LYSODREN is a prescription medicine used to treat people with cancer of the adrenal glands (adrenocortical carcinoma) that is functional (when the adrenal glands make more corticosteroid hormone than normal) or nonfunctional (when the adrenal glands make less corticosteroid hormone than normal) and the cancer cannot be removed by surgery.

Effectiveness in pediatric patients has not been established.

Before taking LYSODREN, tell your healthcare provider about all of your medical conditions, including if you:

have an injury, infection or illness
plan to have surgery. Tell your healthcare providers you are taking LYSODREN. You may need to stop taking LYSODREN before any surgery and dental procedures.
have cysts on your ovaries
have liver or kidney problems
have bleeding problems
are pregnant or plan to become pregnant. LYSODREN can harm your unborn baby.

Females who can become pregnant:

Your healthcare provider will do a pregnancy test before you start treatment with LYSODREN.
Use effective birth control (contraception) that does not contain hormones (nonhormonal) such as condoms or diaphragms and spermicide during treatment with LYSODREN and for as long as your healthcare provider tells you to after you stop treatment.
Talk to your healthcare provider about nonhormonal birth control methods that may be right for you.
Birth control methods that contain hormones such as birth control pills, injections, or patches may not work as well during and after treatment with LYSODREN.
Tell your healthcare provider right away if you become pregnant or think you may be pregnant during treatment with LYSODREN.

are breastfeeding or plan to breastfeed. LYSODREN can pass into your breast milk and may harm your baby. Do not breastfeed during treatment and after you stop taking LYSODREN until your healthcare provider tells you it is okay. Talk to your healthcare provider about the best way to feed your baby during and after treatment with LYSODREN.

Tell your healthcare provider about all the medicines you take, including prescription and over-the-counter medicines, vitamins, and herbal supplements. Taking LYSODREN with certain other medicines may affect the way LYSODREN and the other medicines work and may increase your risk of side effects.

Especially tell your healthcare provider if you take:

spironolactone

hormonal birth control

warfarin

midazolam or other CYP3A substrates

Ask your healthcare provider about any other medicine that may not be listed above.

Know the medicines you take. Keep a list of them to show your healthcare provider and pharmacist when you get a new medicine.

How should I take LYSODREN?

Take LYSODREN exactly as your healthcare provider tells you to take it.
Do not change your dose unless your healthcare provider tells you to.
Take your daily dose of LYSODREN in 3 or 4 divided doses each day.
Swallow LYSODREN tablets whole. Do not crush, chew or split the tablets.
Do not take any LYSODREN tablets that are broken or crushed.
Take LYSODREN with food, preferably a high-fat meal or snack. Talk to your healthcare provider about examples of foods you should eat.
Caregivers should wear disposable gloves when handling LYSODREN tablets. You should avoid contact with crushed or broken tablets. If skin contact with crushed or broken tablets happens, thoroughly wash the skin area right away with soap and water.
If you miss a dose of LYSODREN, skip the missed dose and take the next dose at your regularly scheduled time. Do not take 2 doses at the same time to make up for a missed dose.
If you vomit after taking LYSODREN, take the next dose at your regularly scheduled time.
If you take too much LYSODREN, call your healthcare provider right away or go to the nearest emergency room.

What should I avoid while taking LYSODREN?

Do not drive or operate machinery until you know how LYSODREN affects you. LYSODREN may cause sleepiness, decreased energy, and dizziness, which may affect your ability to drive and operate machinery.

What are the possible side effects of LYSODREN?

LYSODREN can cause serious side effects including:

See “What is the most important information I should know about LYSODREN?”

Neurological problems (central nervous system toxicity). LYSODREN can cause decreased awareness and alertness. See “What should I avoid while taking LYSODREN?” Tell your healthcare provider if you develop any of the following signs and symptoms during treatment or if they get worse:

slow thinking
slow movement or decreased coordination
confusion
difficulty concentrating
memory loss

trouble talking
sleepiness
dizziness
feelings of pins and needles in your hands and feet
feeling very tired

Your healthcare provider may test your blood to make sure your thyroid is producing enough thyroid hormone and to check the mitotane level if you develop any of these signs and symptoms during treatment.

Ovarian cysts in premenopausal women. LYSODREN can cause noncancerous large cysts (macrocysts) on the ovaries of women who have not gone through menopause or just starting menopause (premenopausal). The cysts may cause pain or discomfort in your pelvic area and abnormal periods (menstruation), or they may not cause any symptoms at all. If you are premenopausal, your healthcare provider will do an ultrasound of your ovaries before starting LYSODREN and as needed during treatment. Tell your healthcare provider right away if you develop vaginal bleeding or pelvic pain.
Liver problems. LYSODREN can cause liver problems, including liver injury or liver failure. Tell your healthcare provider right away if you develop any signs and symptoms of liver problems during LYSODREN treatment, including:

yellowing of your skin or the white part of your eyes
dark colored (tea colored) urine
pain in your right upper stomach-area (abdomen)
itching

loss of appetite
nausea, vomiting or diarrhea
bleeding or bruising
tiredness

Low blood cell counts. LYSODREN can cause decreased blood cell counts including decreases in white blood cells, platelets, and red blood cells. This may increase your risk of infection, bleeding, and anemia. Tell your healthcare provider right away if you develop any signs or symptoms of low blood cell counts, including:

fever
trouble breathing
unusual bruising or bleeding

dizziness or lightheadedness
tiredness
pale skin or lightness of skin color

Prolonged bleeding time. LYSODREN can cause bleeding that lasts longer than usual. If you need to have surgery or dental procedures during treatment with LYSODREN, your healthcare provider will do blood tests to check for prolonged bleeding risks. Tell your healthcare provider right away if you develop signs or symptoms of prolonged bleeding during treatment with LYSODREN, including:

unusual bleeding or bleeding that will not stop
bruising
lightheadedness
vomiting blood or your vomit looks like coffee grinds
blood in your stool or black stool that looks like tar

pink or brown urine
coughing up blood or blood clots
menstrual bleeding that is heavier than normal
nose bleeds that happen often

Changes in hormone levels. LYSODREN may cause changes in certain hormone levels in your blood. If you are male, your breasts may swell or become larger during treatment.

Your healthcare provider will do blood tests before you start treatment with LYSODREN, during your treatment, and after you stop treatment with LYSODREN to check mitotane levels in your body and to check for side effects.

Your healthcare provider may change your dose, temporarily stop, or permanently stop treatment with LYSODREN if you develop certain side effects.

The most common side effects of LYSODREN include:

eating disorders (anorexia)
upper stomach area (abdominal) discomfort
nausea
vomiting
diarrhea
depression

dizziness or lightheadedness
rash
high cholesterol
increase of triglycerides (fat in blood)
decreased thyroid hormones
decreased testosterone (in males)

These are not all of the possible side effects of LYSODREN.

Call your doctor for medical advice about side effects. You may report side effects to FDA at 1-800-FDA-1088.

You may also report side effects to Direct Success Inc. at 1-844-597-6373.

How should I store LYSODREN?

Store LYSODREN at 77°F (25°C).

Keep LYSODREN and all medicines out of the reach of children.

General information about the safe and effective use of LYSODREN.

Medicines are sometimes prescribed for purposes other than those listed in a Medication Guide. Do not use LYSODREN for a condition for which it was not prescribed. Do not give LYSODREN to other people, even if they have the same symptoms that you have. It may harm them. You can ask your pharmacist or healthcare provider for information about LYSODREN that is written for health professionals.

What are the ingredients in LYSODREN?

Active ingredient: mitotane

Inactive ingredients: microcrystalline cellulose, polyethylene glycol 3350, silicon dioxide, and starch.

Manufactured by: Latina Pharma S.p.A., Via Murillo, 7, 04013 Sermoneta (Latina), Italy; Manufactured for HRA Pharma Rare Diseases.

For more information, go to www.lysodren.com or call 1-844-597-6373.

This Medication Guide has been approved by the U.S. Food and Drug Administration. Revised: 04/2025

PRINCIPAL DISPLAY PANEL - 100 Tablet Bottle Carton

NDC 76336-080-60

LYSODREN
(mitotane) tablets, for oral use

EACH TABLET CONTAINS
500 mg

100 Tablets
Rx only

HRA Pharma
Rare Diseases